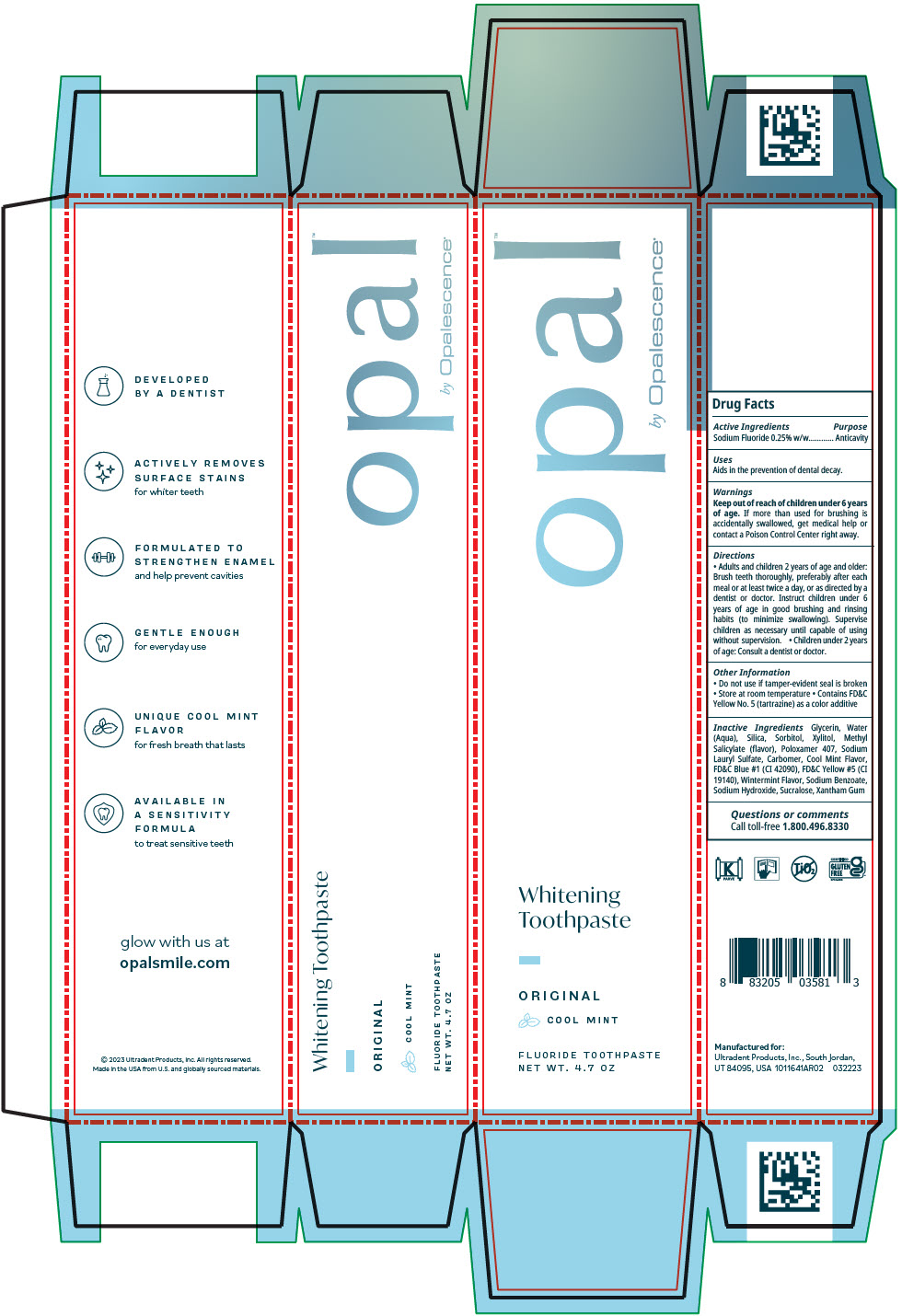 DRUG LABEL: Opal by Opalescence Original
NDC: 51206-312 | Form: GEL, DENTIFRICE
Manufacturer: Ultradent Products, Inc.
Category: otc | Type: HUMAN OTC DRUG LABEL
Date: 20250617

ACTIVE INGREDIENTS: SODIUM FLUORIDE 1.1 mg/1 g
INACTIVE INGREDIENTS: GLYCERIN; WATER; SILICON DIOXIDE; SORBITOL; XYLITOL; METHYL SALICYLATE; POLOXAMER 407; SODIUM LAURYL SULFATE; CARBOMER HOMOPOLYMER TYPE B (ALLYL PENTAERYTHRITOL CROSSLINKED); FD&C BLUE NO. 1; FD&C YELLOW NO. 5; SODIUM BENZOATE; SODIUM HYDROXIDE; SUCRALOSE; XANTHAN GUM

Opal™ by Opalescence®Original

Drug Facts

Active Ingredients

Sodium Fluoride 0.25% w/w

Purpose

Anticavity

Uses

Aids in the prevention of dental decay.

Warnings

Keep out of reach of children under 6 years of age.If more than used for brushing is accidentally swallowed, get medical help or contact a Poison Control Center right away.

Directions

- Adults and children 2 years of age and older: Brush teeth thoroughly, preferably after each meal or at least twice a day, or as directed by a dentist or doctor. Instruct children under 6 years of age in good brushing and rinsing habits (to minimize swallowing). Supervise children as necessary until capable of using without supervision.
- Children under 2 years of age: Consult a dentist or doctor.

Other Information

- Do not use if tamper-evident seal is broken
- Store at room temperature
- Contains FD&C Yellow No. 5 (tartrazine) as a color additive

Inactive Ingredients

Glycerin, Water (Aqua), Silica, Sorbitol, Xylitol, Methyl Salicylate (flavor), Poloxamer 407, Sodium Lauryl Sulfate, Carbomer, Cool Mint Flavor, FD&C Blue #1 (CI 42090), FD&C Yellow #5 (CI 19140), Wintermint Flavor, Sodium Benzoate, Sodium Hydroxide, Sucralose, Xantham Gum

Questions or comments

Call toll-free 1.800.496.8330

PRINCIPAL DISPLAY PANEL - 4.7 OZ Tube Carton

opal™
by Opalescence®

Whitening
Toothpaste

ORIGINAL
COOL MINT

FLUORIDE TOOTHPASTE
NET WT. 4.7 OZ